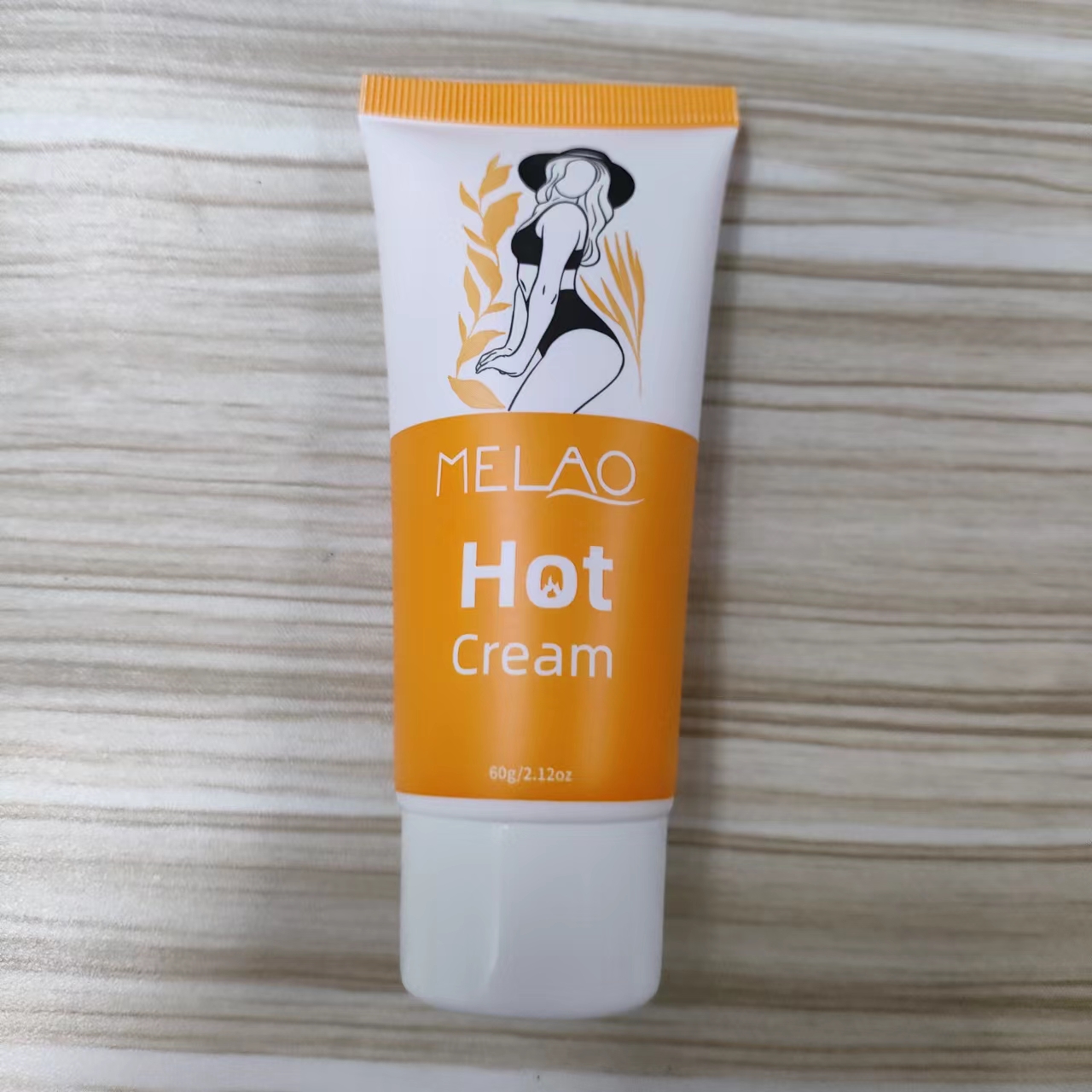 DRUG LABEL: MELAO Hot Cream
NDC: 74458-453 | Form: CREAM
Manufacturer: Guangzhou Yilong Cosmetics Co., Ltd
Category: otc | Type: HUMAN OTC DRUG LABEL
Date: 20241010

ACTIVE INGREDIENTS: VANILLYL BUTYL ETHER 3 g/100 g
INACTIVE INGREDIENTS: PARFUMIDINE; GLYCERIN; SHEANUT OIL; CARBOMER HOMOPOLYMER, UNSPECIFIED TYPE; WATER; ALOE VERA LEAF; HYALURONATE SODIUM; ALLANTOIN; MENTHA X ROTUNDIFOLIA LEAF; CENTELLA ASIATICA TRITERPENOIDS

MELAO Hot Cream (MELAO-W453)

INACTIVE INGREDIENT

Water

Glycerin

Butyrospermum Parkii (Shea) Oil

Mentha Rotundifolia Leaf Extract

Aloe Barbadensis Leaf Extract

Centella Asiatica Extract

Carbomer

Sodium Hyaluronate

Hydrolyzed Collagen

Allantoin

Parfum

ACTIVE INGREDIENT

Vanillyl Butyl Ether

PURPOSE

Promotes fat burning.

INDICATIONS AND USAGE

Apply the massage gel on preferred areas with circular motions. Optionally wrap the area for better results.

WARNINGS

For external use only.

Stop use and ask a doctor if rash occurs.

Do not use on damaged or broken skin.

When using this product keep out of eyes. Rinse with water to remove.

Keep out of reach of children. If swallowed, get medical help or contact a Poison Control Center right away.

DOSAGE AND ADMINISTRATION

Apply the massage gel on preferred areas with circularmotions. Optionally wrap the area for better results.